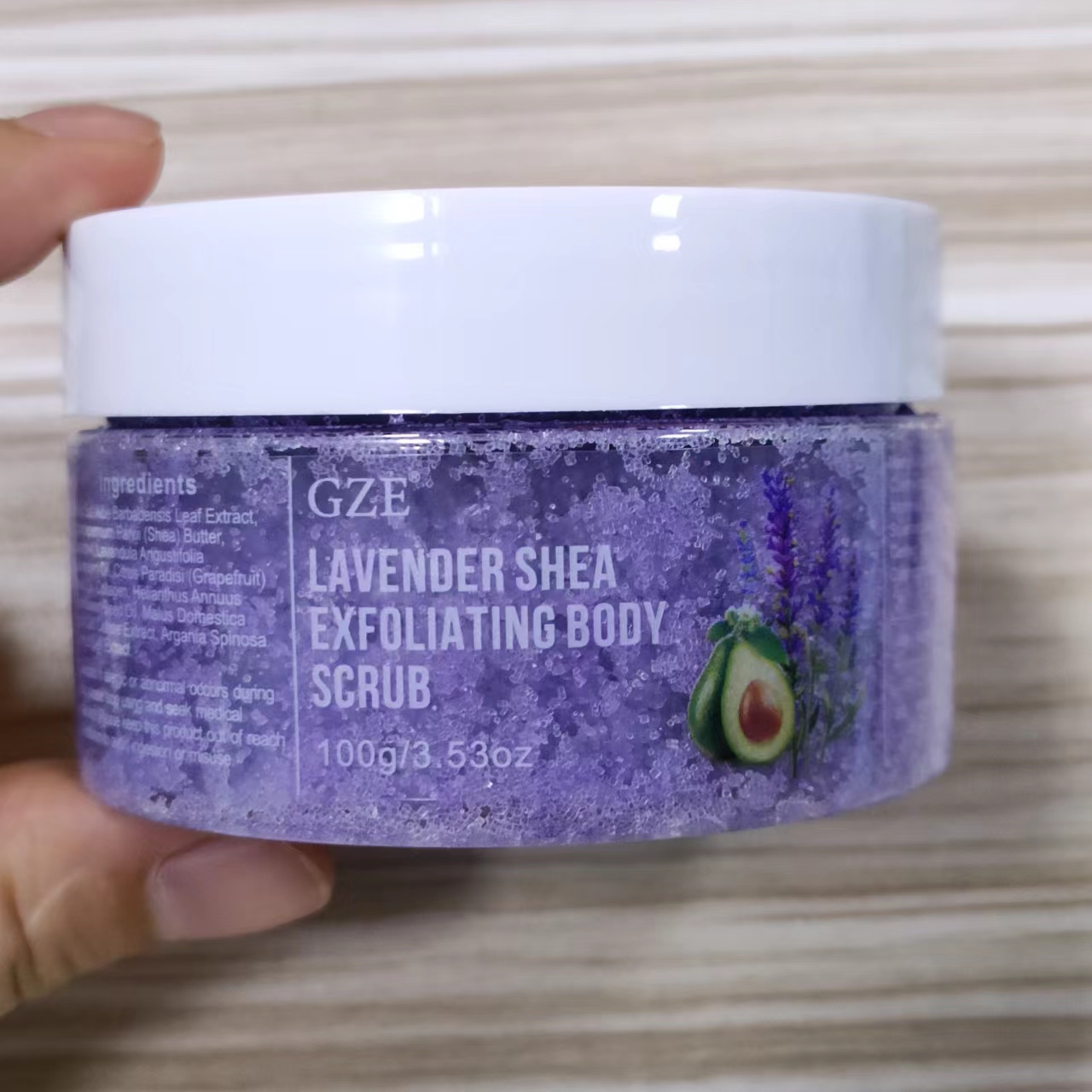 DRUG LABEL: GZE Lavender Shea Exfoliating Body Scrub
NDC: 74458-215 | Form: GRANULE
Manufacturer: Guangzhou Yilong Cosmetics Co., Ltd
Category: otc | Type: HUMAN OTC DRUG LABEL
Date: 20241111

ACTIVE INGREDIENTS: COLLAGENASE 3 2 g/100 g
INACTIVE INGREDIENTS: CITRUS PARADISI (GRAPEFRUIT) SEED OIL; BUTYROSPERMUM PARKII (SHEA) BUTTER; LAURETH-4; MALUS DOMESTICA WHOLE; SEA SALT; HELIANTHUS ANNUUS (SUNFLOWER) SEED OIL; LAVANDULA ANGUSTIFOLIA (LAVENDER) OIL; ALOE BARBADENSIS LEAF EXTRACT

GZE LAVENDER SHEA EXFOLIATING BODY SCRUB

ACTIVE INGREDIENT

Collagen

INACTIVE INGREDIENT

Maris Salt

Aloe Barbadensis Leaf Extract

Butyrospermum Parkii (Shea) Butter

Laureth-4

Lavandula Angustifolia (Lavender) Oil

Citrus Paradisi (Grapefruit) Seed Oil

Helianthus Annuus (Sunflower) Seed Oil

Malus Domestica Fruit Cell Culture Extract

Argania Spinosa Sprout Stem Cell Extract

INDICATIONS AND USAGE

Wash your body, take an appropriate amount of Scrub and apply it to your skin, gently rub in a circle, and finally rinse it off with water, once a month.

DOSAGE AND ADMINISTRATION

Wash your face, take an appropriate amount of Men's Facial Scrub and apply it to your face, gently rub in a circle, and finally rinse it off with water, once a month.

PURPOSE

Exfoliating.

Stop use and ask a doctor if rash occurs.

Do not use on damaged or broken skin.

When using this product keep out of eyes. Rinse with water to remove.

Keep out of reach of children. If swallowed, get medical help or contact a Poison Control Center right away.